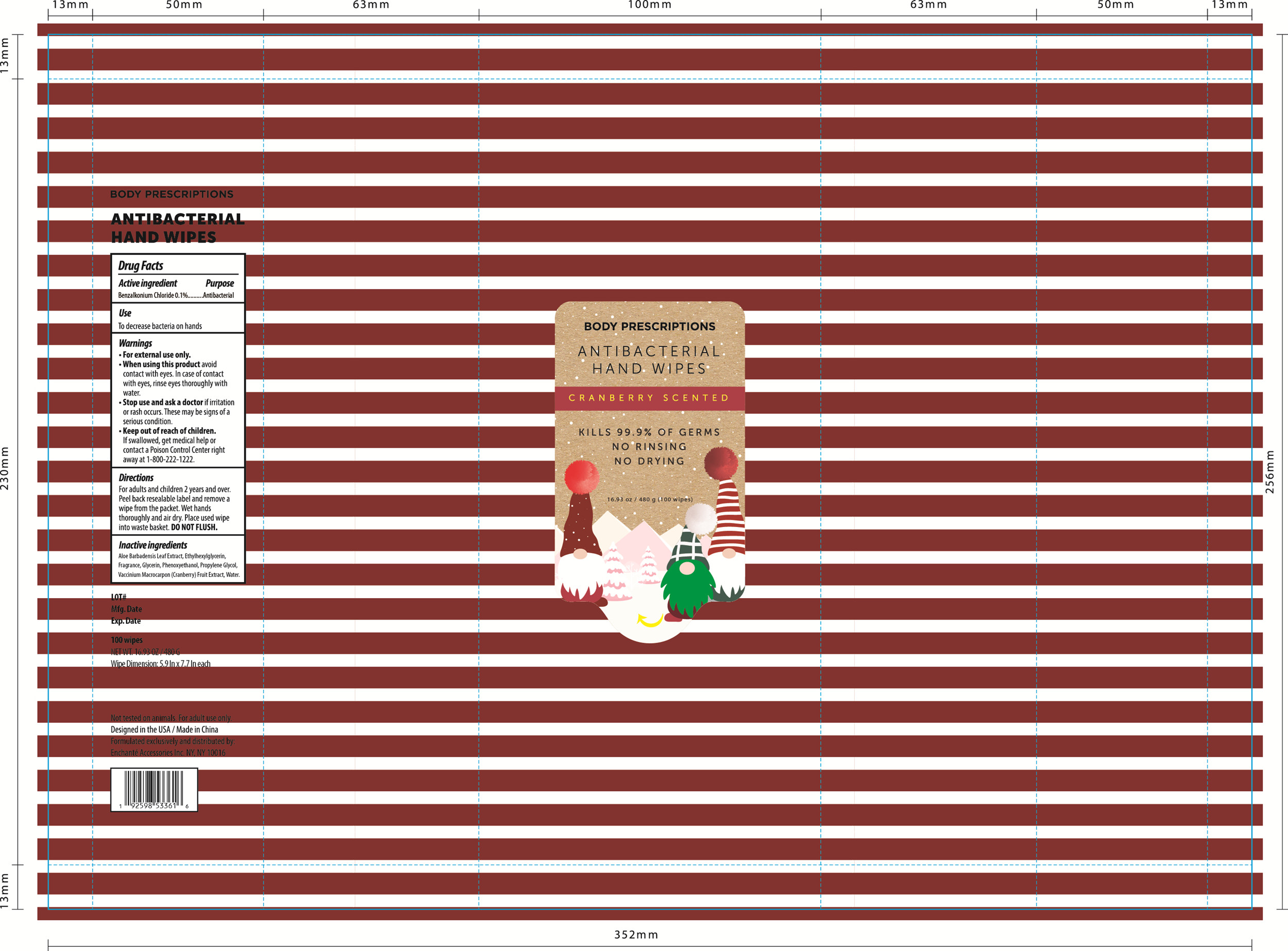 DRUG LABEL: BODY PRESCRIPTIONS ANTIBACTERIAL HAND WIPES CRANBERRY SCENTED
NDC: 50563-369 | Form: SOLUTION
Manufacturer: ENCHANTE ACCESSORIES INC.
Category: otc | Type: HUMAN OTC DRUG LABEL
Date: 20201020

ACTIVE INGREDIENTS: BENZALKONIUM CHLORIDE 3.6 mg/1 1
INACTIVE INGREDIENTS: GLYCERIN; ETHYLHEXYLGLYCERIN; ALOE VERA LEAF; PHENOXYETHANOL; PROPYLENE GLYCOL; WATER; VACCINIUM MACROCARPON WHOLE

50563-369_G0XABW07

Active Ingredient

Benzalkonium Chloride 0.1%

Purpose

Antibacterial

Use

■ To decrease bacteria on hands

WARNINGS

For external use only

When using this product, avoid contact with eyes. In case of contact with eyes, rinse eyes thoroughly with water

Stop use and ask a doctor if irritation or rash occurs. These may be signs of a serious condition.

Keep out of reach of children. If swallowed, get medical help or contact a Poison Control Center right away at 1-800-222-1222

Directions

For adults and children two years and over

Peel over reusable label and remove a wipe from the packet.

Wet hands thoroughly and air dry.

Place used wipes in to waste basket. Do not flush.

Inactive ingredients

Aloe Barbadensis Leaf Extract, Ethylhexylglycerin, Fragrance, Glycerin, Phenoxyethanol, Propylene Glycol, Vaccinium Macrocarpon (Cranberry) Fruit Extract, Water